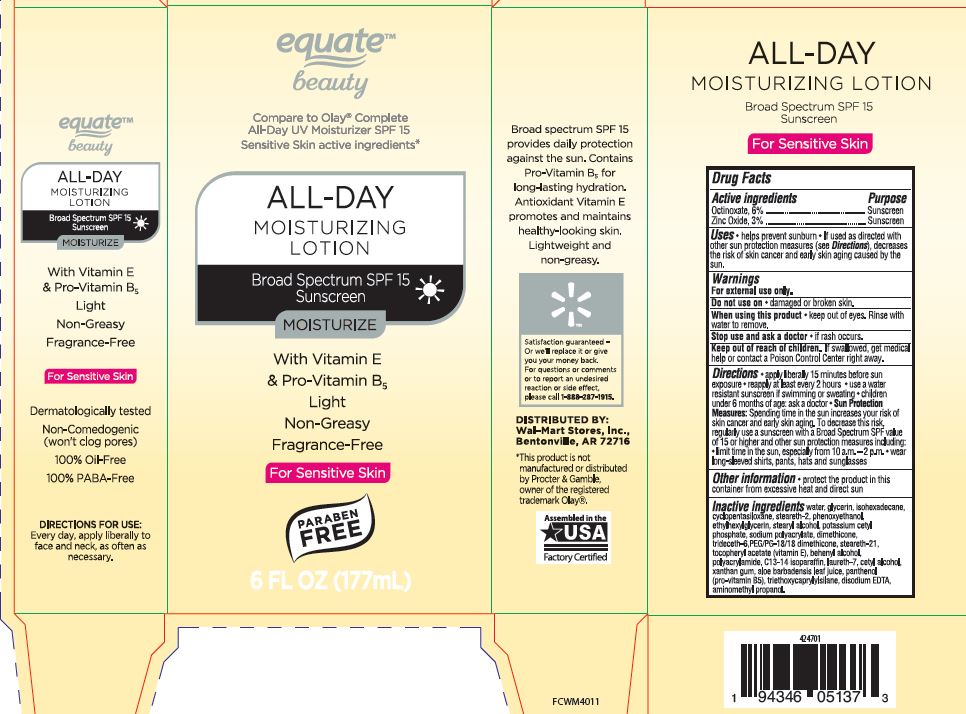 DRUG LABEL: All Day Moisturizing SPF 15
NDC: 79903-210 | Form: LOTION
Manufacturer: Walmart
Category: otc | Type: HUMAN OTC DRUG LABEL
Date: 20260120

ACTIVE INGREDIENTS: OCTINOXATE 6 g/100 mL; ZINC OXIDE 3 g/100 mL
INACTIVE INGREDIENTS: GLYCERIN; TRIETHOXYCAPRYLYLSILANE; ISOHEXADECANE; CYCLOMETHICONE 5; STEARETH-2; PHENOXYETHANOL; ETHYLHEXYLGLYCERIN; STEARYL ALCOHOL; POTASSIUM CETYL PHOSPHATE; SODIUM POLYACRYLATE (8000 MW); DIMETHICONE; TRIDECETH-6; PEG/PPG-18/18 DIMETHICONE; STEARETH-21; .ALPHA.-TOCOPHEROL ACETATE; DOCOSANOL; CETYL ALCOHOL; POLYACRYLAMIDE (1500 MW); C13-14 ISOPARAFFIN; LAURETH-7; ALOE; SODIUM BENZOATE; POTASSIUM SORBATE; XANTHAN GUM; EDETATE DISODIUM ANHYDROUS; PANTHENOL; AMINOMETHYLPROPANOL

PLSF-1844 EQB All Day Moisturizing Lotion SPF 15 (DMI)

Active ingredients Purpose

Octinoxate, 6% Sunscreen
Zinc Oxide, 3% Sunscreen

Uses

•helps prevent sunburn• If used as directed with other sun protection measures (see Oirections),decreases the risk of skin cancer and early skin aging caused by the sun.

Do not use on

• damaged or broken skin.

When using this product

•keep out of eyes. Rinse with waterto remove.

Stop use and ask a doctor

• if rash occurs.

Directions:

• apply liberal 15 minutes before sun exposure• reapply at least every 2 hours •use a water resistant sunscreen if swimmingor sweating•children under 6 months of age: ask a doctor• Sun Protection Measures:Spending time in the sun increase your risk of skin cancer and early skin aging. To decrease this risk. regularly usea sunscreen wrtha Broad Spectrum SPF value of15 or higher and other suncrin protection measures including:
• limrt time in the sun, especial from 10a.m. -2 p.rn.•wear long-sleeve shorts , pants, hats and sunglasses

Inactive Ingredients:

Water
Xanthan Gum
Disodium EDTA
Glycerin
Isohexadecane
Cyclopentasiloxane
Steareth-21
Stearyl Alcohol
Cetyl Alcohol
Steareth-2
Potassium Cetyl Phosphate
Octinoxate
Zinc Oxide, Triethoxycaprylylsilane
Tocopheryl Acetate
Behenyl Alcohol
Phenoxyethanol, Ethylhexylglycerin
Panthenol
Polyacrylamide, C13-14 Isoparaffin, Laureth-7
Sodium Polyacrylate, Dimethicone, Cyclopentasiloxane, Trideceth-6, PEG/PPG-18/18 Dimethicone
Aminomethyl Propanol
Aloe Barbadensis (Aloe Vera) Leaf Juice, Sodium Benzoate, Potassium Sorbate